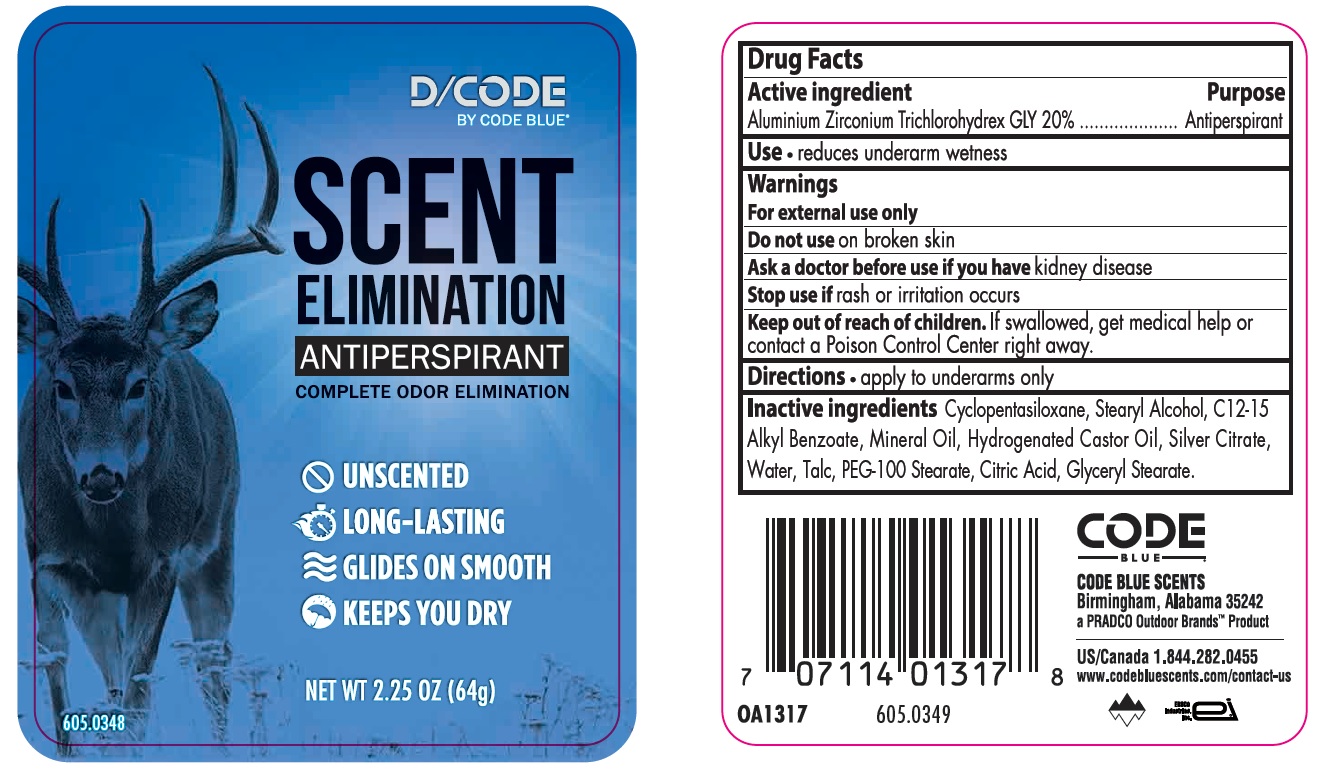 DRUG LABEL: Code Blue Scent Elimination
NDC: 10889-423 | Form: STICK
Manufacturer: VVF Kansas Services LLC
Category: otc | Type: HUMAN OTC DRUG LABEL
Date: 20171222

ACTIVE INGREDIENTS: ALUMINUM ZIRCONIUM TRICHLOROHYDREX GLY 20 g/100 g
INACTIVE INGREDIENTS: STEARYL ALCOHOL; HYDROGENATED CASTOR OIL; CYCLOMETHICONE 5; MINERAL OIL; SILVER CITRATE; ALKYL (C12-15) BENZOATE; WATER; TALC; PEG-100 STEARATE; CITRIC ACID MONOHYDRATE; GLYCERYL STEARATE SE

Code Blue Scent Elimination

Active ingredient

Aluminum Zirconium Trichlorohydrex GLY 20%

Purpose

Antiperspirant

Uses

- reduces underarm wetness

Warnings

For external use only

Do not use on broken skin

Ask a doctor before use if you have kidney disease

Stop use if rash or irritation occurs

Keep out of reach of children.

If swallowed, get medical help or contact a Poison Control Center right away.

Directions

- apply to underarms only

Inactive ingredients

Cyclopentasiloxane, Stearyl Alcohol, C12-15 Alkyl Benzoate,

Mineral Oil, Hydrogenated Castor Oil, Silver Citrate, Water,

Talc, PEG-100 Stearate, Citric Acid, Glyceryl Stearate

CODE BLUE

CODE BLUE SCENTS

Birmingham, Alabama 35242

a PRADCO Outdoor Brands ™ Product

QUESTIONS

US/Canada 1.844.282.0455

www.codebluescents.com/contact-us

D/CODE

BY CODE BLUE

SCENT ELIMINATION

ANTIPERSPIRANT

COMPLETE ODOR ELIMINATION

- UNSCENTED
- LONG LASTING
- GLIDES ON SMOOTH
- KEEPS YOU DRY

NET WT 2.25 OZ (64g)